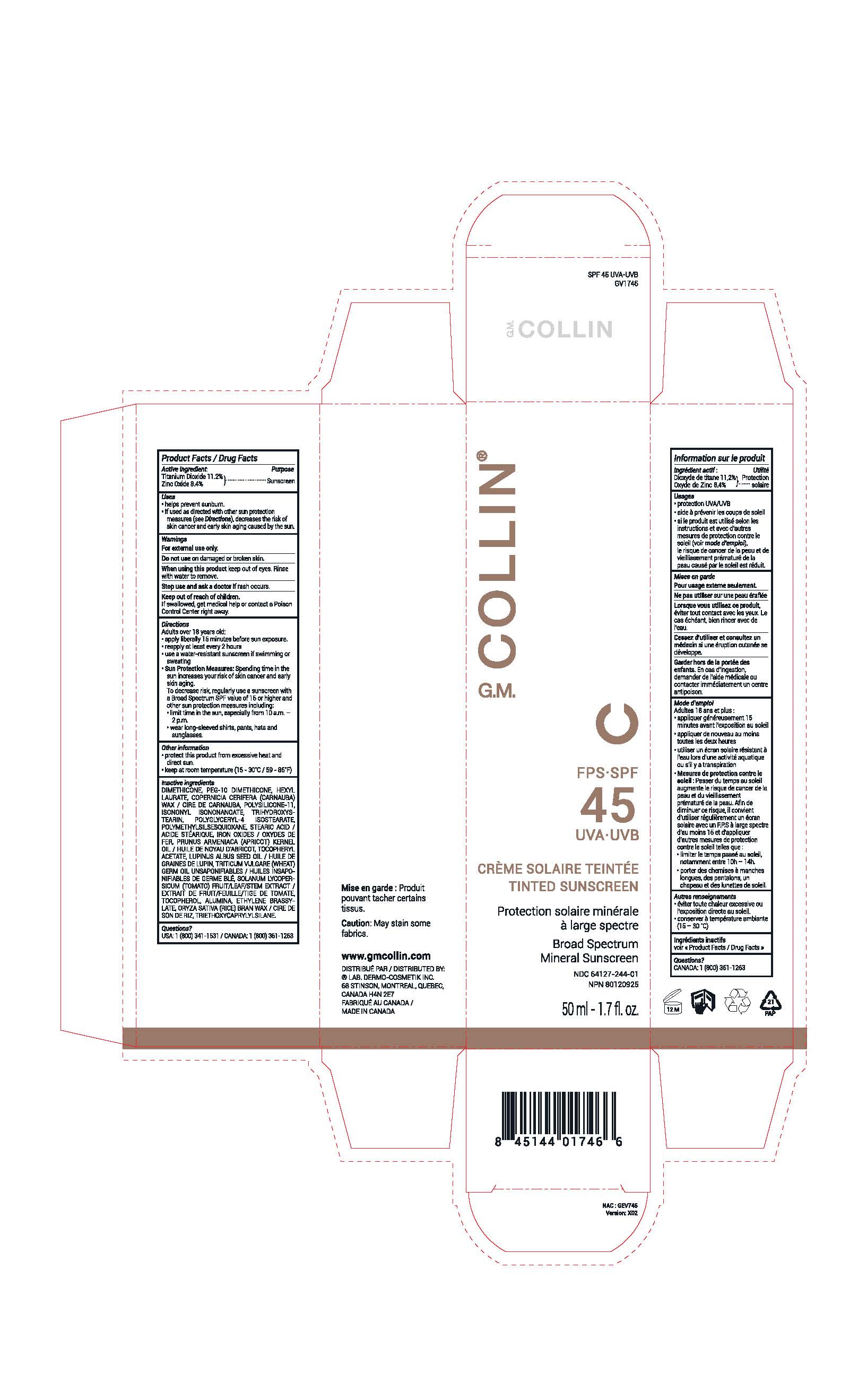 DRUG LABEL: G.M. Collin FPS-SPF 45 UVA-UVB TINTED SUNSCREEN
NDC: 64127-244 | Form: CREAM
Manufacturer: LABORATOIRES DERMO-COSMETIK INC.
Category: otc | Type: HUMAN OTC DRUG LABEL
Date: 20251209

ACTIVE INGREDIENTS: ZINC OXIDE 8.4 g/100 g; TITANIUM DIOXIDE 11.2 g/100 g
INACTIVE INGREDIENTS: ALUMINUM OXIDE; ETHYLENE BRASSYLATE; SOLANUM LYCOPERSICUM FRUITING TOP; ALPHA-TOCOPHEROL ACETATE; RICE BRAN; FERRIC OXIDE YELLOW; FERRIC OXIDE RED; FERROSOFERRIC OXIDE; APRICOT KERNEL OIL; LUPINUS ALBUS SEED OIL; TRIETHOXYCAPRYLYLSILANE; DIMETHICONE; DIMETHICONE/VINYL DIMETHICONE CROSSPOLYMER (SOFT PARTICLE); WHEAT GERM OIL UNSAPONIFIABLES; TRIHYDROXYSTEARIN; HEXYL LAURATE; CARNAUBA WAX; PEG-10 DIMETHICONE (220 CST); POLYMETHYLSILSESQUIOXANE (4.5 MICRONS); STEARIC ACID; ISONONYL ISONONANOATE; POLYGLYCERYL-4 ISOSTEARATE; TOCOPHEROL

GM Collin SPF45 TINTED SUNSCREEN

Product Facts / Drug Facts

Active ingredient:

Titanium Dioxide 11.2%
Zinc Oxide 8.4%

Purpose

Sunscreen

Uses

• helps prevent sunburn.
• if used as directed with other sun protection
measures (see Directions), decreases the risk of
skin cancer and early skin aging caused by the sun.

Warnings

For external use only.

Do not use on damaged or broken skin.

When using this product keep out of eyes. Rinse
with water to remove.

Stop use and ask a doctor if rash occurs.

Keep out of reach of children.
If swallowed, get medical help or contact a Poison
Control Center right away.

Directions

Adults over 18 years old:
• apply liberally 15 minutes before sun exposure.
• reapply at least every 2 hours
• use a water-resistant sunscreen if swimming or sweating
• Sun Protection Measures: Spending time in the sun increases your risk of skin cancer and early skin aging.
To decrease risk, regularly use a sunscreen with a Broad Spectrum SPF value of 15 or higher and other sun protection measures including:
• limit time in the sun, especially from 10 a.m. – 2 p.m.
• wear long-sleeved shirts, pants, hats and sunglasses.

Other information

• protect this product from excessive heat and direct sun.
• keep at room temperature (15 - 30˚C / 59 - 86˚F)

Inactive ingredients

DIMETHICONE, PEG-10 DIMETHICONE, HEXYL LAURATE, COPERNICIA CERIFERA (CARNAUBA) WAX / CIRE DE CARNAUBA, POLYSILICONE-11, ISONONYL ISONONANOATE, TRIHYDROXYSTEARIN, POLYGLYCERYL-4 ISOSTEARATE, POLYMETHYLSILSESQUIOXANE, STEARIC ACID / ACIDE STÉARIQUE, IRON OXIDES / OXYDES DE FER, PRUNUS ARMENIACA (APRICOT) KERNEL OIL / HUILE DE NOYAU D’ABRICOT, TOCOPHERYL ACETATE, LUPINUS ALBUS SEED OIL / HUILE DE GRAINES DE LUPIN, TRITICUM VULGARE (WHEAT) GERM OIL UNSAPONIFIABLES / HUILES INSAPONIFIABLES DE GERME BLÉ, SOLANUM LYCOPERSICUM (TOMATO) FRUIT/LEAF/STEM EXTRACT / EXTRAIT DE FRUIT/FEUILLE/TIGE DE TOMATE, TOCOPHEROL, ALUMINA, ETHYLENE BRASSYLATE, ORYZA SATIVA (RICE) BRAN WAX / CIRE DE SON DE RIZ, TRIETHOXYCAPRYLYLSILANE.

Questions?

USA: 1 (800) 341-1531 / CANADA: 1 (800) 361-1263

www.gmcollin.com
DISTRIBUÉ PAR / DISTRIBUTED BY:
® LAB. DERMO-COSMETIK INC.
68 STINSON, MONTREAL, QUEBEC,
CANADA H4N 2E7
FABRIQUÉ AU CANADA /
MADE IN CANADA